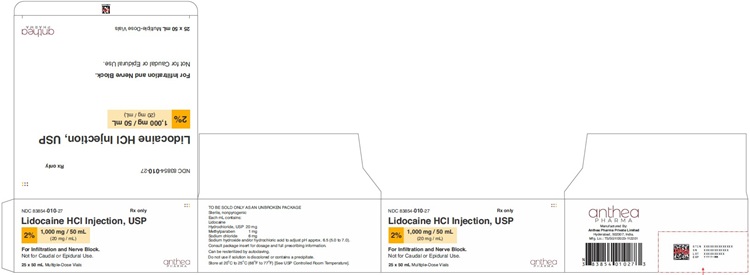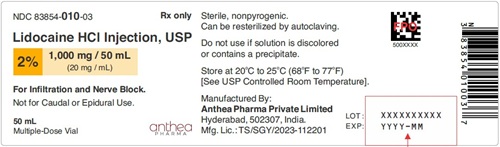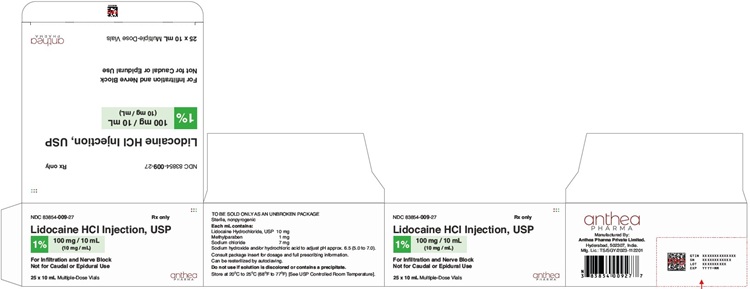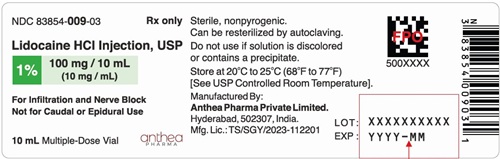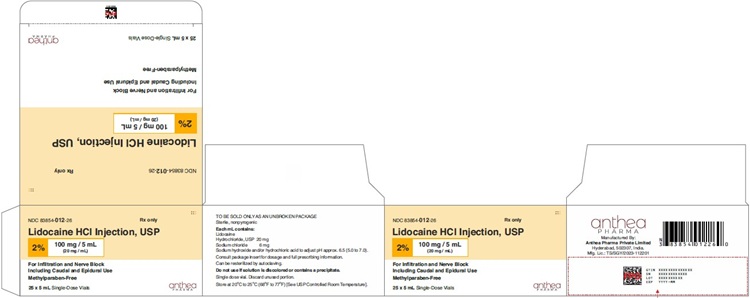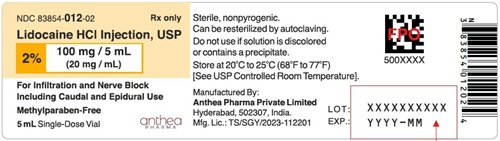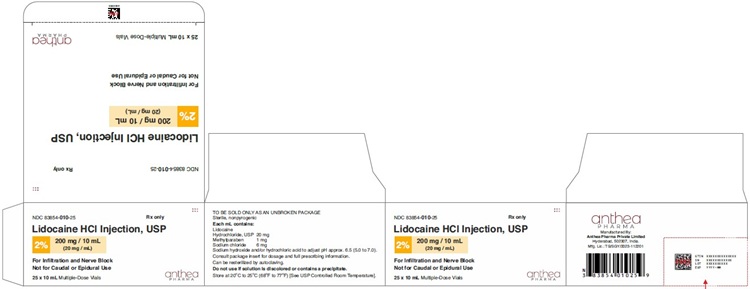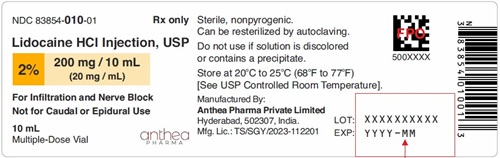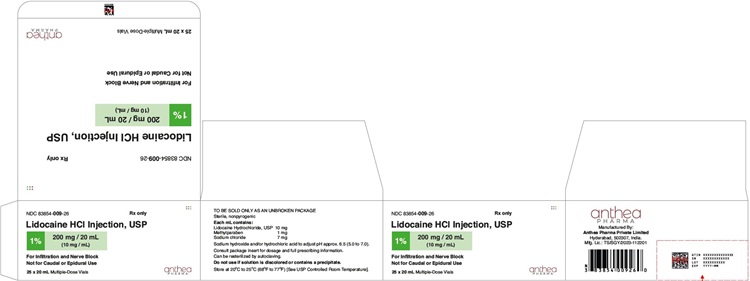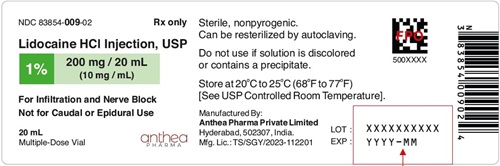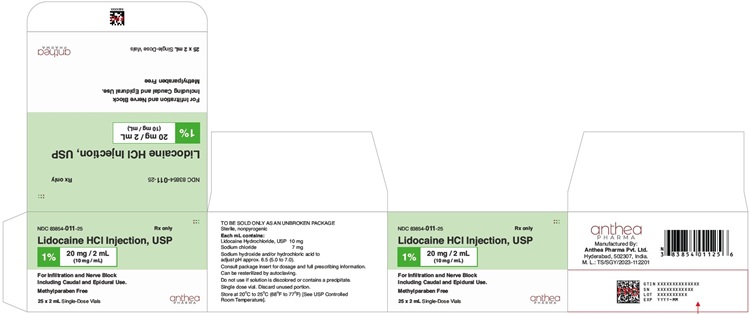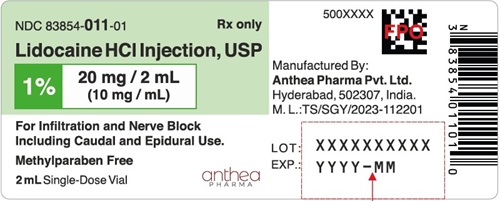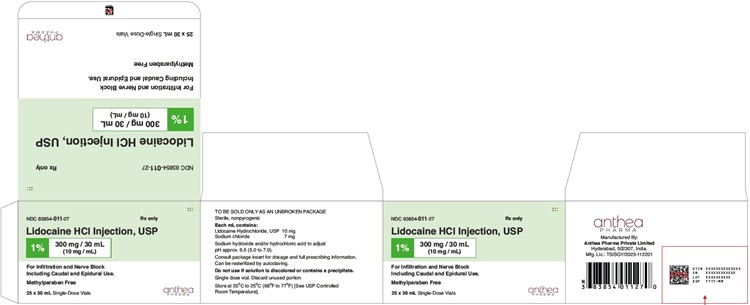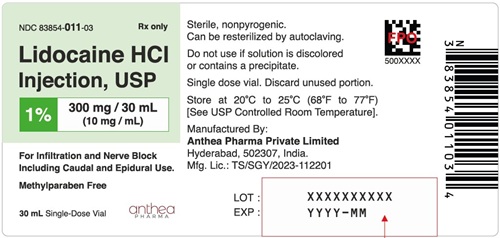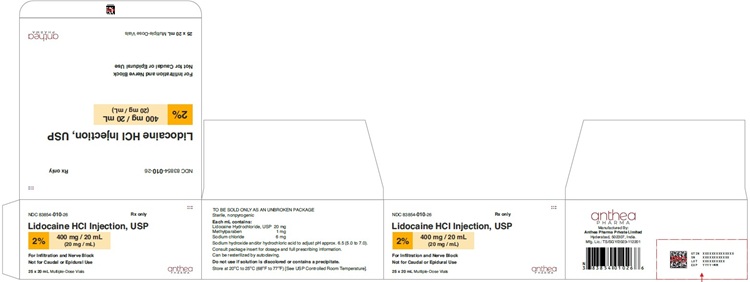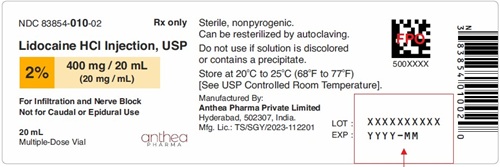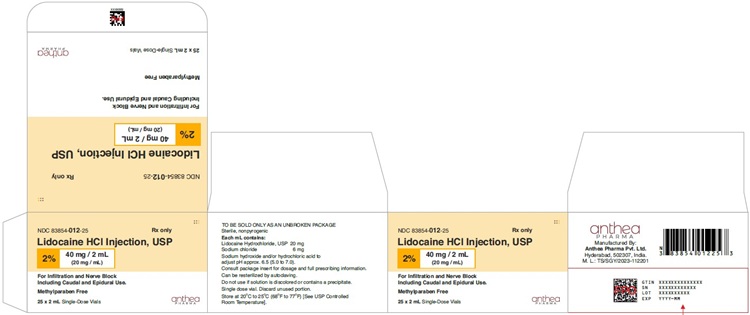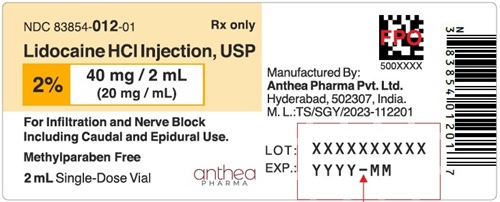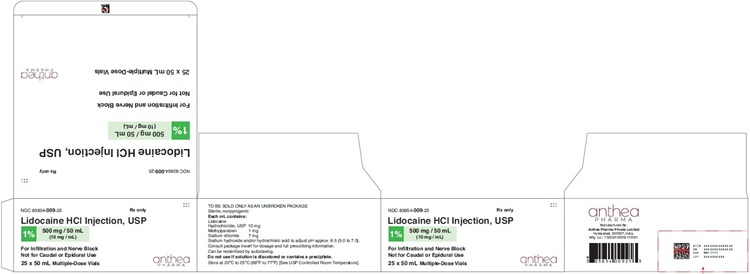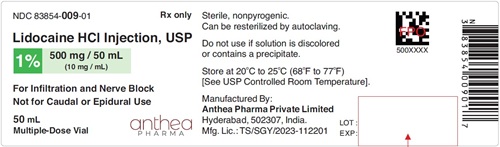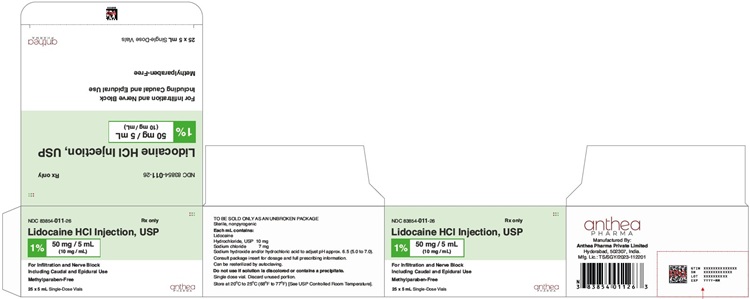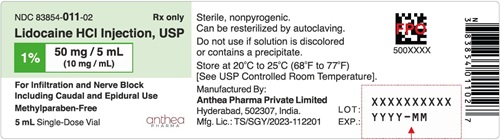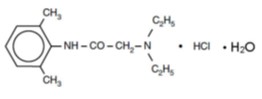 DRUG LABEL: Lidocaine Hydrochloride
NDC: 83854-009 | Form: INJECTION, SOLUTION
Manufacturer: Anthea Pharma Private Limited
Category: prescription | Type: HUMAN PRESCRIPTION DRUG LABEL
Date: 20260209

ACTIVE INGREDIENTS: LIDOCAINE HYDROCHLORIDE 10 mg/1 mL

HIGHLIGHTS OF PRESCRIBING INFORMATION

These highlights do not include all the information needed to use
LIDOCAINE HYDROCHLORIDE INJECTION safely and effectively. See full prescribing information for LIDOCAINE HYDROCHLORIDE INJECTIONS.
LIDOCAINE HYDROCHLORIDE injection, for infiltration and nerve block.
LIDOCAINE HYDROCHLORIDE injection – MPF (Methyl Paraben Free), for infiltration, nerve block, epidural and caudal.
Initial U.S. Approval: 1948

1 INDICATIONS AND USAGE

Lidocaine hydrochloride injection contains lidocaine, an amide local anesthetic. Lidocaine hydrochloride injection is indicated in adult and pediatric patients for the production of local or regional anesthesia or analgesia for surgery, dental, and oral surgery procedures, diagnostic and therapeutic procedures, and for obstetrical procedures. For each type of block indicated to produce local or regional anesthesia or analgesia, specific concentrations and presentations are recommended. (1, 2.2)

2 DOSAGE AND ADMINISTRATION

- See Full Prescribing Information for recommended dosages and administration information for adult and pediatric patients

3 DOSAGE FORMS AND STRENGTHS

- Lidocaine hydrochloride injection, USP: 1%, 2%
- Lidocaine hydrochloride Injection, USP (MPF): 1%, 2%

4 CONTRAINDICATIONS

- Known hypersensitivity to any local anesthetic agent of the amide-type or to other components of lidocaine hydrochloride injection.

5 WARNINGS AND PRECAUTIONS

- Dose-Related Toxicity: Monitor cardiovascular and respiratory vital signs and patient’s state of consciousness after injection of lidocaine hydrochloride injection (5.1)
- Methemoglobinemia: Cases of methemoglobinemia have been reported in association with local anesthetics use. See full prescribing information for more details on managing these risks. (5.2)
- Chondrolysis with Intra-Articular Infusion:Avoid Intra-articular infusions as there have been post-marketing reports of chondrolysis in patients receiving such infusion. (5.4)
- Allergic-Type Reactions to Sulfites in Lidocaine Hydrochloride Injection and Anaphylactic Reactions:Lidocaine hydrochloride injection without epinephrine does not contain sodium metabisulfite (5.6)
- Risk of Systemic Toxicities with Unintended Intravascular or Intrathecal Injection: Unintended intravascular or intrathecal injection may be associated with systemic toxicities, including CNS or cardiorespiratory depression and coma, progression ultimately to respiratory arrest. Aspirate for blood or cerebrospinal fluid (where applicable) prior to each dose and consider using a test dose of lidocaine hydrochloride injection (5.7)

6 ADVERSE REACTIONS

Most common adverse reactions are as follows:

- Central Nervous System: Lightheadedness, nervousness, apprehension, euphoria, confusion, dizziness, drowsiness, tinnitus, blurred or double vision, vomiting, sensations of heat, cold or numbness, twitching, tremors, convulsions, unconsciousness, respiratory depression and arrest. (6)
- Cardiovascular System: Bradycardia, hypotension, and cardiovascular collapse. (6)
- Allergic: Cutaneous lesions, urticaria, edema or anaphylactoid reactions. (6)
- Neurologic: Positional headaches, hypotension and backache. (6)
- Hematologic: Methemoglobinemia. (6)

To report SUSPECTED ADVERSE REACTIONS, contact Anthea Pharma Private Limited at 1-8xx-xxxxxxx or FDA at 1-800-FDA-1088 or www.fda.gov/medwatch

7 DRUG INTERACTIONS

- Local Anesthetics: The toxic effects of local anesthetics are additive. Monitor for neurologic and cardiovascular effects when additional local anesthetics are administered (7.1)
- Monoamine Oxidase Inhibitors and Tricyclic Antidepressants: Administration of lidocaine hydrochloride injection to patients receiving monoamine oxidase inhibitors or tricyclic antidepressants may produce severe, prolonged hypertension Concurrent use of these agents should generally be avoided (5.5, 7.2)
- Ergot-type Oxytocic drugs: Concurrent administration of lidocaine hydrochloride injection and ergot-type oxytocic drugs may cause severe, persistent hypertension or cerebrovascular accidents (5.5, 7.3)
- Nonselective Beta-Adrenergic Antagonists:Administration of lidocaine hydrochloride injection in patients receiving nonselective beta-adrenergic antagonist may cause severe hypertension and bradycardia. Concurrent use of these agents should generally be avoided. (5.5, 7.4)
- Drugs Associated with Methemoglobinemia: Patients are at increased risk of developing methemoglobinemia when concurrently exposed to nitrates, nitrites, local anesthetics, antineoplastic agents, antibiotics, antimalarials, anticonvulsants and other drugs (7.5).
- Geriatric Use: Elderly patients should be given reduced doses commensurate with their age and physical condition (8.5)
- Hepatic Impairment: consider reduced dosing and increased monitoring for local anesthetic systemic toxicity in patients with hepatic impairment (8.6)

FULL PRESCRIBING INFORMATION

1 INDICATIONS AND USAGE

Lidocaine hydrochloride injection is indicated in adult and pediatric patients for the production of local or regional anesthesia or analgesia for surgery, dental, and oral surgery procedures, diagnostic and therapeutic procedures, and for obstetrical procedures. Specific concentrations and presentations of lidocaine hydrochloride injection is recommended for each type of block indicated to produce local or regional or anesthesia or analgesia [see Dosage and Administration (2.2)].

2 DOSAGE AND ADMINISTRATION

2.1 Important Dosage and Administration Information

- Lidocaine hydrochloride injection is not recommended for intrathecal use.
- Avoid use of lidocaine hydrochloride injection solutions containing antimicrobial preservatives (i.e., multiple-dose vials) for epidural or caudal anesthesia [see Warnings and Precautions (5.3)].
- Discard unused portions of solution not containing preservatives, i.e., those supplied in single-dose vials, following initial use.
- Visually inspect this product for particulate matter and discoloration prior to administration whenever solution and container permit. Lidocaine hydrochloride injection is a clear, colorless solutions. Do not administer solutions which are discolored or contain particulate matter.
- Parenteral drug products should be inspected visually for particulate matter and discoloration prior to administration whenever the solution and container permit. Solutions which are discolored (e.g., pinkish or darker than slightly yellow) or which contain particulate matter or precipitate should not be administered.
- Mixing or the prior or intercurrent use of any other local anesthetic with Lidocaine hydrochloride injection is not recommended because of insufficient data on the clinical use of such mixtures.

Administration Precautions

- Lidocaine hydrochloride injection is to be administered in carefully adjusted dosages by or under the supervision of experienced clinicians who are well versed in the diagnosis and management of dose-related toxicity and other acute emergencies which might arise from the block to be employed.
- Use lidocaine hydrochloride injection only if the following are immediately available: oxygen, cardiopulmonary resuscitative equipment and drugs, and the personnel resources needed for proper management of toxic reactions and related emergencies [see Warnings and Precautions (5.1), Adverse Reactions (6), Overdosage (10)].
- The toxic effects of local anesthetics are additive. Monitor for neurologic and cardiovascular effects related to local anesthetic systemic toxicity when additional local anesthetics are administered with lidocaine hydrochloride injection [see Warnings and Precautions (5.1), Drug Interactions (7.1), Overdosage (10)].
- Aspirate for blood or cerebrospinal fluid (where applicable) prior to injecting lidocaine hydrochloride injection, both the initial dose and all subsequent doses, to avoid intravascular or intrathecal injection. However, a negative aspiration for blood or cerebrospinal fluid does not ensure against an intravascular or intrathecal injection [see Warnings and Precautions (5.7)].
- Avoid rapid injection of a large volume of lidocaine hydrochloride injection and use fractional (incremental) doses when feasible.
- During major regional nerve blocks, such as those of the brachial plexus or lower extremity, the patient should have an indwelling intravenous catheter to assure adequate intravenous access. The lowest dosage of lidocaine hydrochloride injection that results in effective anesthesia should be used to avoid high plasma levels and serious adverse reactions.
- Perform careful and constant monitoring of cardiovascular and respiratory (adequacy of oxygenation and ventilation) vital signs and the patient’s level of consciousness after each local anesthetic injection.
- Use lidocaine hydrochloride injection in carefully restricted quantities in areas of the body supplied by end arteries or having otherwise compromised blood supply such as digits, nose, external ear, or penis.

2.2 Recommended Concentrations and Dosages of lidocaine hydrochloride injection in Adults

The dosage of lidocaine hydrochloride injection administered varies with the anesthetic procedure, the area to be anesthetized, the vascularity of the tissues, the number of neuronal segments to be blocked, the depth of anesthesia and degree of muscle relaxation required, the duration of anesthesia desired, individual tolerance, and the physical condition of the patient. Administer the smallest dosage and concentration required to produce the desired result.

The types of block and recommended lidocaine hydrochloride injection concentrations are shown in Table 1. The dosages suggested in this table are for normal healthy adults and refer to the use of epinephrine-free solutions. Consider administration of solutions containing epinephrine when large volumes are required.

Table 1: Recommended Dosages in Adults

Procedure | Lidocaine Hydrochloride Injection
Procedure | Conc (%) | Vol (mL) | Total Dose (mg)
Infiltration
Percutaneous | 0.5 or 1 | 1 to 60 | 5 to 300
Intravenous regional | 0.5 | 10 to 60 | 50 to 300**
Peripheral Nerve Blocks, e.g.,
Brachial | 1.5 | 15 to 20 | 225 to 300
Dental | 2 | 1 to 5 | 20 to 100
Intercostal | 1 | 3 | 30
Paravertebral | 1 | 3 to 5 | 30 to 50
Pudendal (each side) | 1 | 10 | 100
Paracervical
Obstetrical analgesia
(each side) | 1 | 10 | 100
Sympathetic Nerve Blocks, e.g.,
Cervical (stellate ganglion) | 1 | 5 | 50
Lumbar | 1 | 5 to 10 | 50 to 100
Central Neural Blocks
Epidural*
Thoracic | 1 | 20 to 30 | 200 to 300
Lumbar
Analgesia | 1 | 25 to 30 | 250 to 300
Anesthesia | 1.5 | 15 to 20 | 225 to 300
 | 2 | 10 to 15 | 200 to 300
Caudal
Obstetrical analgesia | 1 | 20 to 30 | 200 to 300
Surgical anesthesia | 1.5 | 15 to 20 | 225 to 300

*Dose determined by number of dermatomes to be anesthetized (2 to 3 mL/dermatome).
** Dose should not exceed 4 mg/kg.

The above suggested concentrations and volumes serve only as a guide. Other volumes and concentrations may be used provided the total maximum recommended dose is not exceeded.

These recommended doses serve only as a guide to the amount of local anesthetic required for most indicated procedures. The actual volumes and concentrations to be used depend on a number of factors such as type and extent of surgical procedure, depth of anesthesia and degree of muscular relaxation required, duration of anesthesia required, and the physical condition of the patient. In all cases, the lowest concentration and smallest dose that will produce the desired result should be given. The maximum dosage limit within the recommended dosage range must be individualized in each case after evaluating the size and physical status of the patient, as well as the anticipated rate of systemic absorption from a particular injection site.

2.3 Use in Epidural Anesthesia

During epidural administration, administer lidocaine hydrochloride injection, 1% (10 mg/mL) and 2% (20 mg/mL) solutions in incremental doses of 3 mL to 5 mL with sufficient time between doses to detect toxic manifestations of unintentional intravascular or intrathecal injection. Administer injections slowly, with frequent aspirations before and during the injection to avoid intravascular injection. Perform syringe aspirations before and during each supplemental injection in continuous (intermittent) catheter techniques. Repeat doses of lidocaine hydrochloride injection should be preceded by a test dose containing epinephrine if not clinically contraindicated. Use only the single-dose vials for caudal or epidural anesthesia; avoid use of the multiple-dose vials for these procedures, which contain a preservative [see Dosage and Administration (2.1, 2.4), Warnings and Precautions (5.7)].

2.4 Test Dose for Epidural Blocks

In the event of the known injection of a large volume of local anesthetic solution into the subarachnoid space, after suitable resuscitation and if the catheter is in place, consider attempting the recovery of drug by draining a moderate amount of cerebrospinal fluid (such as 10 mL) through the epidural catheter.

2.6 Maximum Recommended Dosage

Adults

For normal healthy adults, the maximum individual dose should not exceed 4.5 mg/kg of body weight, and in general it is recommended that the maximum total dose does not exceed 300 mg. For continuous epidural or caudal anesthesia, the maximum recommended dosage should not be administered at intervals of less than 90 minutes. When continuous lumbar or caudal epidural anesthesia is used for non-obstetrical procedures, a higher total dose may be administered if required to produce adequate anesthesia.

The maximum recommended dose per 90 minute period of lidocaine hydrochloride for paracervical block in obstetrical patients and non-obstetrical patients is 200 mg total. One half of the total dose is usually administered to each side. Inject slowly, five minutes between sides [see Pregnancy (8.1)].

Pediatric Patients

A maximum dose of lidocaine hydrochloride injection for children varies based on age and weight. For children over 3 years of age with a normal lean body mass and normal body development, the maximum dose is determined by the child’s age and weight. For example, in a child of 5 years weighing approximately 23 kg, the dose of lidocaine hydrochloride should not exceed approximately 75 mg to 100 mg (3.3 mg/kg to 4.4 mg/kg). The use of dilute solutions (i.e., 0.25% to 0.5%) and total dosages not to exceed 3 mg/kg are recommended for induction of intravenous regional anesthesia in children.

The lowest effective concentration and lowest effective dose should be used. Dilution of available concentrations with 0.9% sodium chloride injection may be required to obtain the required final concentration.

3 DOSAGE FORMS AND STRENGTHS

Lidocaine hydrochloride injection, USP is a clear, colorless solution available as:

- 1% (500 mg per 50 mL) (10 mg per mL), 50 mL multiple-dose vials
- 1% (200 mg per 20 mL) (10 mg per mL), 20 mL multiple-dose vials
- 1% (100 mg per 10 mL) (10 mg per mL), 10 mL multiple-dose vials
- 2% (200 mg per 10 mL) (20 mg per mL), 10 mL multiple-dose vials
- 2% (400 mg per 20 mL) (20 mg per mL), 20 mL multiple-dose vials
- 2% (1000 mg per 50 mL) (20 mg per mL), 50 mL multiple-dose vials

Lidocaine hydrochloride injection - MPF* is a clear colorless solution available as:

- 1% (20 mg per 2 mL) (10 mg per mL), 2 mL single-dose vials
- 1% (50 mg per 5 mL) (10 mg per mL), 5 mL single-dose vials
- 1% (300 mg per 30 mL) (10 mg per mL), 30 mL single-dose vials
- 2% (40 mg per 2 mL) (20 mg per mL), 2 mL single-dose vials
- 2% (100 mg per 5 mL) (20 mg per mL), 5 mL single-dose vials

*Dosage forms listed as Lidocaine hydrochloride injection - MPF indicate single dose solutions that are Methylparaben Free (MPF).

4 CONTRAINDICATIONS

Lidocaine hydrochloride injection is contraindicated in patients with a known hypersensitivity to lidocaine or to any local anesthetics of the amide type or to other components of lidocaine hydrochloride injection.

5 WARNINGS AND PRECAUTIONS

5.1 Dose-Related Toxicity

The safety and effectiveness of lidocaine hydrochloride injection depend on proper dosage, correct technique, adequate precautions, and readiness for emergencies. Careful and constant monitoring of cardiovascular and respiratory (adequacy of ventilation) vital signs and the patient's state of consciousness should be performed after injection of lidocaine hydrochloride solutions.

Possible early warning signs of central nervous system (CNS) toxicity are restlessness, anxiety, incoherent speech, lightheadedness, numbness and tingling of the mouth and lips, metallic taste, tinnitus, dizziness, blurred vision, tremors, twitching, CNS depression, or drowsiness. Delay in proper management of dose-related toxicity, underventilation from any cause, and/or altered sensitivity may lead to the development of acidosis, cardiac arrest, and, possibly, death.

During major regional nerve blocks, such as those of the brachial plexus or lower extremity, the patient should have an indwelling intravenous catheter to assure adequate intravenous access. Use the lowest dosage of lidocaine hydrochloride injection that results in effective anesthesia to avoid high plasma levels and serious adverse effects. Avoid rapid injection of a large volume of lidocaine hydrochloride injection solution and administer fractional (incremental) doses when feasible.

Injection of repeated doses of lidocaine hydrochloride injection may cause significant increases in plasma levels with each repeated dose due to slow accumulation of the drug or its metabolites, or to slow metabolic degradation. Tolerance to elevated blood levels varies with the status of the patient. Debilitated, elderly patients and acutely ill patients should be given reduced doses commensurate with their age and physical status.

5.2 Methemoglobinemia

Cases of methemoglobinemia have been reported in association with local anesthetic use. Although all patients are at risk for methemoglobinemia, patients with glucose-6-phosphate dehydrogenase deficiency, congenital or idiopathic methemoglobinemia, cardiac or pulmonary compromise, infants under 6 months of age, and concurrent exposure to oxidizing agents or their metabolites are more susceptible to developing clinical manifestations of the condition [see Drug Interactions (7.5)]. If local anesthetics must be used in these patients, close monitoring for symptoms and signs of methemoglobinemia is recommended.

Signs of methemoglobinemia may occur immediately or may be delayed some hours after exposure and are characterized by a cyanotic skin discoloration and abnormal coloration of the blood. Methemoglobin levels may continue to rise; therefore, immediate treatment is required to avert more serious central nervous system and cardiovascular adverse effects, including seizures, coma, arrhythmias, and death. Discontinue lidocaine hydrochloride injection and any other oxidizing agents. Depending on the severity of the symptoms, patients may respond to supportive care, i.e., oxygen therapy, hydration. More severe symptoms may require treatment with methylene blue, exchange transfusion, or hyperbaric oxygen.

5.3 Antimicrobial Preservatives in Multiple-Dose Vials

Avoid use of lidocaine hydrochloride injection solutions containing antimicrobial preservatives (i.e., those supplied in multiple-dose vials) for epidural or caudal anesthesia because safety has not been established with such use.

5.4 Chondrolysis with Intra-Articular Infusion

Intra-articular infusions of local anesthetics following arthroscopic and other surgical procedures is an unapproved use, and there have been post-marketing reports of chondrolysis in patients receiving such infusions. The majority of reported cases of chondrolysis have involved the shoulder joint; cases of gleno-humeral chondrolysis have been described in pediatric and adult patients following intra-articular infusions of local anesthetics with and without epinephrine for periods of 48 to 72 hours. There is insufficient information to determine whether shorter infusion periods are not associated with these findings. The time of onset of symptoms, such as joint pain, stiffness and loss of motion can be variable, but may begin as early as the 2nd month after surgery. Currently, there is no effective treatment for chondrolysis; patients who experienced chondrolysis have required additional diagnostic and therapeutic procedures and some required arthroplasty or shoulder replacement.

5.5 Risk of Adverse Reactions Due to Drug Interactions with lidocaine hydrochloride injection

Risk of Severe, Persistent Hypertension Due to Drug Interactions Between lidocaine hydrochloride injection and Monoamine Oxidase Inhibitors and Tricyclic Antidepressants

Administration of lidocaine hydrochloride injection in patients receiving monoamine oxidase inhibitors (MAOI), or tricyclic antidepressants may result in severe, prolonged hypertension. Concurrent use of these agents should generally be avoided. In situations when concurrent therapy is necessary, careful monitoring of the patient's hemodynamic status is essential [see Drug Interactions (7.2)].

Risk of Severe, Persistent Hypertension or Cerebrovascular Accidents Due to Drug Interactions Between lidocaine hydrochloride injection and Ergot-Type Oxytocic Drugs

Concurrent administration of lidocaine hydrochloride injection and ergot-type oxytocic drugs may cause severe, persistent hypertension or cerebrovascular accidents. Avoid use of lidocaine hydrochloride injection concomitantly with ergot-type oxytocic drugs [see Drug Interactions (7.3)].

Risk of Hypertension and Bradycardia Due to Drug Interactions Between lidocaine hydrochloride injection and Nonselective Beta-Adrenergic Antagonists

Administration of lidocaine hydrochloride injection in patients receiving nonselective beta-adrenergic antagonists may cause severe hypertension and bradycardia. Concurrent use of these agents should generally be avoided. In situations when concurrent therapy is necessary, careful monitoring of the patient's blood pressure and heart rate is essential [see Drug Interactions (7.4)]

5.6 Allergic-Type Reactions to Sulfite in Lidocaine Hydrochloride Injection and Anaphylactic Reactions

Lidocaine hydrochloride injection without epinephrine does not contain sodium metabisulfite.

Anaphylactic reactions may occur following administration of lidocaine hydrochloride [see Adverse Reactions (6)]. Lidocaine hydrochloride should be used with caution in persons with known drug sensitivities. Patients allergic to para-aminobenzoic acid derivatives (procaine, tetracaine, benzocaine, etc.) have not shown cross-sensitivity to lidocaine hydrochloride.

5.7 Risk of Systemic Toxicities with Unintended Intravascular or Intrathecal Injection

Unintended intravascular or intrathecal injection of lidocaine hydrochloride injection may be associated with systemic toxicities, including CNS or cardiorespiratory depression and coma, progressing ultimately to respiratory arrest. Unintentional intrathecal injection during the intended performance of nerve blocks near the vertebral column has resulted in underventilation or apnea ("Total or High Spinal"). A high spinal has been characterized by paralysis of the legs, loss of consciousness, respiratory paralysis, and bradycardia [see Adverse Reactions (6)].

Aspirate for blood or cerebrospinal fluid (where applicable) before injecting lidocaine hydrochloride injection, both the initial dose and all subsequent doses, to avoid intravascular or intrathecal injection. However, a negative aspiration for blood or cerebrospinal fluid does not ensure against an intravascular or intrathecal injection.

5.8 Risk of Toxicity in Patients with Hepatic Impairment

Because amide local anesthetics such as lidocaine are metabolized by the liver, consider reduced dosing and increased monitoring for lidocaine systemic toxicity in patients with moderate to severe hepatic impairment who are treated with lidocaine hydrochloride injection, especially with repeat doses [see Use in Specific Populations (8.6)].

5.9 Risk of Use in Patients with Impaired Cardiovascular Function

Lidocaine hydrochloride injection should also be given in reduced doses in patients with impaired cardiovascular function since they may be less able to compensate for functional changes associated with the prolongation of A-V conduction produced by these drugs. Monitor patients closely for blood pressure, heart rate, and ECG changes.

5.12 Risk of Adverse Reactions with Use in the Head and Neck Area

Small doses of local anesthetics (e.g., lidocaine hydrochloride injection) injected into the head and neck area, including retrobulbar, dental and stellate ganglion blocks, may produce adverse reactions similar to systemic toxicity seen with unintentional intravascular injections of larger doses. The injection procedures require the utmost care. Confusion, convulsions, respiratory depression and/or respiratory arrest, and cardiovascular stimulation or depression have been reported. These reactions may be due to intraarterial injection of the local anesthetic with retrograde flow to the cerebral circulation. They may also be due to puncture of the dural sheath of the optic nerve during retrobulbar block with diffusion of any local anesthetic along the subdural space to the midbrain. Monitor circulation and respiration and constantly observe patients receiving lidocaine hydrochloride injection blocks. Resuscitative equipment and drugs, and personnel for treating adverse reactions should be immediately available. Dosage recommendations should not be exceeded [see Dosage and Administration (2.2)].

5.13 Familial Malignant Hyperthermia

Many drugs used during the conduct of anesthesia are considered potential triggering agents for familial malignant hyperthermia. Since it is not known whether amide-type local anesthetics may trigger this reaction and since the need for supplemental general anesthesia cannot be predicted in advance, it is suggested that a standard protocol for the management of malignant hyperthermia should be available. Early unexplained signs of tachycardia, tachypnea, labile blood pressure and metabolic acidosis may precede temperature elevation. Successful outcome is dependent on early diagnosis, prompt discontinuance of the suspect triggering agent(s) and institution of treatment, including oxygen therapy, indicated supportive measures and dantrolene (consult dantrolene sodium intravenous package insert before using).

5.14 Risk of Respiratory Arrest with Use in Ophthalmic Surgery

Clinicians who perform retrobulbar blocks should be aware that there have been reports of respiratory arrest following local anesthetic injection. Prior to retrobulbar block (e.g., with lidocaine hydrochloride injection), as with all other regional procedures, resuscitative equipment and drugs, and personnel to manage respiratory arrest or depression, convulsions, and cardiac stimulation or depression should be immediately available [see Warnings and Precautions (5.14)]. As with other anesthetic procedures, patients should be constantly monitored following ophthalmic blocks for signs of these adverse reactions, which may occur following relatively low total doses.

5.16 Drug/Laboratory Test Interactions

The intramuscular injection of lidocaine HCl may result in an increase in creatine phosphokinase levels. Thus, the use of this enzyme determination, without isoenzyme separation, as a diagnostic test for the presence of acute myocardial infarction may be compromised by the intramuscular injection of lidocaine HCl.

6 ADVERSE REACTIONS

The following clinically significant adverse reactions have been reported and described in the Warnings and Precautions section of the labeling:

- Dose-Related Toxicity [see Warnings and Precautions (5.1)]
- Methemoglobinemia [see Warnings and Precautions (5.2)]
- Chondrolysis with Intra-Articular Infusion [see Warnings and Precautions (5.4)]
- Severe, Persistent Hypertension, Cerebrovascular Accidents, and Bradycardia Due to Drug Interactions [see Warnings and Precautions (5.5)]
- Allergic-Type Reactions [see Warnings and Precautions (5.6)]
- Systemic Toxicities with Unintended Intravascular or Intrathecal Injection [see Warnings and Precautions (5.7)]
- Respiratory Arrest Following Retrobulbar Block [see Warnings and Precautions (5.14)]

The following adverse reactions from voluntary reports or clinical studies have been reported with lidocaine or lidocaine and epinephrine. Because many of these reactions were reported voluntarily from a population of uncertain size, it is not always possible to reliably estimate their frequency or establish a causal relationship to drug exposure.

Adverse reactions to lidocaine hydrochloride injection is characteristic of those associated with other amide-type local anesthetic. A major cause of adverse reactions to this group of drugs is excessive plasma levels, which may be due to overdosage, unintentional intravascular injection, or slow metabolic degradation.

The most commonly encountered acute adverse reactions that demand immediate counter measures were related to the CNS and the cardiovascular system. These adverse reactions were generally dose-related and due to high plasma levels which may have resulted from overdosage, rapid absorption from the injection site, diminished tolerance, or from unintentional intravascular injection of the local anesthetic solution. In addition to systemic does-related toxicity, unintentional intrathecal injection of drug during the intended performance of caudal or lumbar epidural block or nerve blocks near the vertebral column (especially in the head and neck region) has resulted in underventilation or apnea (“Total or High Spinal”). Also, hypertension due to loss of sympathetic tone and respiratory paralysis or underventilation due to cephalad extension of the motor level of anesthesia have occurred. This has led to secondary cardiac arrest when untreated.

When used for dental injections, paresthesia of the lips, tongue, and oral tissues have been reported. Persistent paresthesia lasting weeks to months and, in some instances, lasting greater than one year, have also been reported.

Nervous System Disorders

Adverse reactions were characterized by excitation and/or depression of the central nervous system and included lightheadedness, nervousness, apprehension, euphoria, confusion, dizziness, drowsiness, tinnitus, blurred or double vision, vomiting, sensations of heat, cold or numbness, twitching, tremors, convulsions, unconsciousness, respiratory depression and arrest.
The incidences of adverse reactions associated with the use of local anesthetics may be related to the total dose of local anesthetic administered and are also dependent upon the particular drug used, the route of administration and the physical status of the patient. In a prospective review of 10,440 patients who received lidocaine hydrochloride for spinal anesthesia, the incidences of adverse reactions were reported to be about 3 percent each for positional headaches, hypotension and backache; 2 percent for shivering; and less than 1 percent each for peripheral nerve symptoms, nausea, respiratory inadequacy and double vision.

Persistent motor, sensory and/or autonomic (sphincter control) deficit of some lower spinal segments with slow recovery (several months) or incomplete recovery have been reported in rare instances when caudal or lumbar epidural block has been attempted. Backache and headache have also been noted following use of these anesthetic procedures.

There have been reported cases of permanent injury to extraocular muscles requiring surgical repair following retrobulbar administration.

In the practice of caudal or lumbar epidural block, unintentional penetration of the subarachnoid space by the catheter or needle has occurred. Subsequent adverse effects may have depended partially on the amount of drug administered intrathecally and the physiological and physical effects of a dural puncture. A high spinal has been characterized by paralysis of the legs, loss of consciousness, respiratory paralysis, and bradycardia.

Neurologic effects following epidural or caudal anesthesia have included spinal block of varying magnitude (including high or total spinal block); hypotension secondary to spinal block; urinary retention; fecal and urinary incontinence; loss of perineal sensation and sexual function; persistent anesthesia, paresthesia, weakness, paralysis of the lower extremities and loss of sphincter control, all of which had slow, incomplete, or no recovery; headache; backache; septic meningitis; meningismus; slowing of labor; increased incidence of forceps delivery; and cranial nerve palsies due to traction on nerves from loss of cerebrospinal fluid.

Neurologic effects following other procedures or routes of administration have included persistent anesthesia, paresthesia, weakness, paralysis, all with slow, incomplete, or no recovery.

Convulsions: Incidence varied with the procedure used and the total dose administered. In a survey of studies of epidural anesthesia, overt toxicity progressing to convulsions occurred in approximately 0.1% of local anesthetic administrations. The incidences of adverse neurologic reactions associated with the use of local anesthetics may be related to the total dose of local anesthetic administered and are also dependent upon the particular drug used, the route of administration, and the physical status of the patient.

Cardiac Disorders: High doses or unintentional intravascular injection have led to high plasma levels and related depression of the myocardium, decreased cardiac output, heartblock, hypotension, bradycardia, ventricular arrhythmias, including ventricular tachycardia and ventricular fibrillation, and cardiac arrest [see Warnings and Precautions (5.9)].

Immune System Disorders

Allergic reactions are characterized by cutaneous lesions, urticaria, edema or anaphylactoid reactions. Allergic reactions may occur as a result of sensitivity either to local anesthetic agents or to the methylparaben used as a preservative in the multiple dose vials. [see Warnings and Precautions (5.6)].

There have been no reports of cross sensitivity between lidocaine hydrochloride and procainamide or between lidocaine hydrochloride and quinidine.

Hematologic

Methemoglobinemia [See Warnings and Precautions (5.2)].

7 DRUG INTERACTIONS

7.1 Local Anesthetics

The toxic effects of local anesthetics are additive. If coadministration of other local anesthetics with lidocaine hydrochloride injection cannot be avoided, monitor patients for neurologic and cardiovascular effects related to local anesthetic systemic toxicity [see Warnings and Precautions (5.1)].

7.2 Monoamine Oxidase Inhibitors and Tricyclic Antidepressants

The administration of lidocaine hydrochloride injection to patients receiving monoamine oxidase inhibitors or tricyclic antidepressants may produce severe, prolonged hypertension. Concurrent use of these agents should generally be avoided. In situation when concurrent therapy is necessary, careful monitoring of the patient’s hemodynamic status is essential [see Warnings and Precautions (5.5)].

7.3 Ergot-Type Oxytocic Drugs

Concurrent administration of vasopressor drugs (for the treatment of hypotension related to obstetric blocks) and ergot-type oxytocic drugs may cause severe, persistent hypertension or cerebrovascular accidents. Avoid use of lidocaine hydrochloride injection concomitantly with ergot-type oxytocic drugs [see Warnings and Precautions (5.5)].

7.4 Nonselective Beta-Adrenergic Antagonists

Administration of lidocaine hydrochloride injection in patients receiving nonselective beta-adrenergic antagonists may cause severe hypertension and bradycardia. Concurrent use of these agents should generally be avoided. In situations when concurrent therapy is necessary, careful monitoring of the patient's blood pressure and heart rate is essential [see Warnings and Precautions (5.5)].

7.5 Drugs Associated with Methemoglobinemia

Patients that are administered local anesthetics may be at increased risk of developing methemoglobinemia when concurrently exposed to the following oxidizing agents:

Class | Examples
Nitrates/Nitrites | nitroglycerin, nitroprusside, nitric oxide, nitrous oxide
Local anesthetics | articaine, benzocaine, bupivacaine, lidocaine, mepivacaine, prilocaine, procaine, ropivacaine, tetracaine
Antineoplastic agents | cyclophosphamide, flutamide, rasburicase, ifosfamide, hydroxyurea
Antibiotics | dapsone, sulfonamides, nitrofurantoin, para- aminosalicylic acid
Antimalarials | chloroquine, primaquine
Anticonvulsants | phenytoin, sodium valproate, phenobarbital
Other drugs | acetaminophen, metoclopramide, quinine, sulfasalazine

8 USE IN SPECIFIC POPULATIONS

8.1 Pregnancy

Risk Summary

Available published data and decades of clinical use with lidocaine hydrochloride injection in pregnant women have not identified any drug associated risk for major birth defects, miscarriage, or other adverse maternal or fetal outcomes. Local anesthetics may cause varying degrees of toxicity to the mother and fetus and adverse reactions include alterations of the central nervous system, peripheral vascular tone and cardiac function (see Clinical Considerations).

In a published animal reproduction study, pregnant rats administered lidocaine by continuous subcutaneous infusion at a dose approximately 9.6 times the maximum recommended human dose (MRHD) of 500 mg in lidocaine hydrochloride injection during the period of organogenesis resulted in lower fetal body weights [see Data].

The estimated background risk of major birth defects and miscarriage for the indicated population is unknown. All pregnancies have a background risk of birth defects, loss, or other adverse outcomes. In the United States general population, the estimated background risks of major birth defects and miscarriage in clinically recognized pregnancies is 2% to 4% and 15%to 20%, respectively. Clinical Considerations

Maternal adverse reactions

Maternal hypotension has resulted from regional anesthesia. Local anesthetics produce vasodilation by blocking sympathetic nerves. Therefore, during treatment of systemic toxicity, maternal hypotension or fetal bradycardia following regional block, the parturient should be maintained in the left lateral decubitus position if possible or manual displacement of the uterus off the great vessels be accomplished. Elevating the patient’s legs will also help prevent decreases in blood pressure. The fetal heart rate also should be monitored continuously, and electronic fetal monitoring is highly advisable.

Labor or delivery

Local anesthetics rapidly cross the placenta, and when used for epidural, paracervical, pudendal or caudal block anesthesia, can cause varying degrees of maternal, fetal and neonatal toxicity [see Clinical Pharmacology (12.3)]. The incidence and degree of toxicity depend upon the procedure performed, the type and amount of drug used, and the technique of drug administration. Adverse reactions in the parturient, fetus and neonate involve alterations of the central nervous system, peripheral vascular tone and cardiac function. However, dosage recommendations for spinal anesthesia are much lower than dosage recommendations for other major blocks.

Spinal anesthesia may alter the forces of parturition through changes in uterine contractility or maternal expulsive efforts. Spinal anesthesia has also been reported to prolong the second stage of labor by removing the parturient’s reflex urge to bear down or by interfering with motor function. The use of obstetrical anesthesia may increase the need for forceps assistance. The use of some local anesthetic drug products during labor and delivery may be followed by diminished muscle strength and tone for the first day or two of life.

Data

Animal Data

Reproduction studies have been performed in rats at doses up to 6.6 times the human dose and have revealed no evidence of harm to the fetus caused by lidocaine hydrochloride.

In a published study, lidocaine administered to pregnant rats by continuous subcutaneous infusion during the period of organogenesis at 100, 250, and 500 mg/kg/day, did not produce any structural abnormalities, but did result in lower fetal weights at 500 mg/kg/day dose (approximately 9.6 times the maximum recommended human dose [MRHD] of 500 mg lidocaine on a mg/m2 basis) in the absence of maternal toxicity.

8.2 Lactation

Risk Summary

Published data report the presence of lidocaine and its metabolites in human milk in low amounts, along with poor oral bioavailability. There are no data on the effect of lidocaine on the breastfed infant or the effect on milk production. The developmental and health benefits of breastfeeding should be considered along with the mother’s clinical need for lidocaine hydrochloride injection.

Injection and any potential adverse effects on the breastfed child from lidocaine hydrochloride injection or from the underlying maternal condition.

8.4 Pediatric Use

Dosages in children should be reduced, commensurate with age, body weight and physical condition [see Dosage and Administration (2.6)].

8.5 Geriatric Use

Elderly patients should be given reduced doses commensurate with their age and physical condition. [see Dosage and Administration (2.6)].

8.6 Hepatic Impairment

Amide-type local anesthetics such as lidocaine are metabolized by the liver. Patients with severe hepatic impairment, because of their inability to metabolize local anesthetics normally, are at greater risk of developing toxic plasma concentrations and potentially local anesthetic systemic toxicity. Therefore, consider reduced dosing and increased monitoring for local anesthetic systemic toxicity in patients with hepatic impairment treated with lidocaine hydrochloride injection, especially with repeat doses [see Warnings and Precautions (5.8)]

10 OVERDOSAGE

Clinical Presentation

Acute emergencies from local anesthetics are generally related to high plasma levels encountered during therapeutic use of local anesthetics or to unintended subarachnoid injection of local anesthetic solution [see Warnings and Precautions (5.1) and see Adverse Reactions (6)].

Management

The first consideration is prevention, best accomplished by careful and constant monitoring of cardiovascular and respiratory vital signs and the patient’s state of consciousness after each local anesthetic injection. At the first sign of change, oxygen should be administered.

The first step in the management of convulsions, as well as underventilation or apnea due to unintended subarachnoid injection of drug solution, consists of immediate attention to the maintenance of a patent airway and assisted or controlled ventilation with oxygen and a delivery system capable of permitting immediate positive airway pressure by mask. Immediately after the institution of these ventilatory measures, the adequacy of the circulation should be evaluated, keeping in mind that drugs used to treat convulsions sometimes depress the circulation when administered intravenously. Should convulsions persist despite adequate respiratory support, and if the status of the circulation permits, a benzodiazepine (such as diazepam) may be administered intravenously. The clinician should be familiar, prior to the use of local anesthetics, with these anticonvulsant drugs. Supportive treatment of circulatory depression may require administration of intravenous fluids and, when appropriate, a vasopressor as directed by the clinical situation (e.g., ephedrine).

If not treated immediately, both convulsions and cardiovascular depression can result in hypoxia, acidosis, bradycardia, arrhythmias and cardiac arrest. Underventilation or apnea due to unintentional subarachnoid injection of local anesthetic solution may produce these same signs and also lead to cardiac arrest if ventilatory support is not instituted. If cardiac arrest should occur, standard cardiopulmonary resuscitative measures should be instituted.

Endotracheal intubation, employing drugs and techniques familiar to the clinician, may be indicated, after initial administration of oxygen by mask, if difficulty is encountered in the maintenance of a patent airway or if prolonged ventilatory support (assisted or controlled) is indicated.

Dialysis is of negligible value in the treatment of acute overdosage with lidocaine hydrochloride.

11 DESCRIPTION

Lidocaine hydrochloride injection, USP contains lidocaine hydrochloride, an amide local anesthetic, as the active pharmaceutical ingredient. The route of administration for lidocaine hydrochloride injection, USP is by injection, for infiltration, nerve block, epidural and caudal use. Multiple dose vials contain methylparaben and they should not be used for caudal and lumbar epidural blocks. Dosage forms listed as lidocaine hydrochloride injection, USP - MPF indicate single-dose solutions that are Methylparaben Free (MPF).

Lidocaine hydrochloride, is chemically designated as acetamide, 2-(diethylamino)-N-(2,6-dimethylphenyl)-, monohydrochloride monohydrate and has the molecular weight of 288.8 g/mol. Lidocaine hydrochloride molecular formula is C14H22N2O • HCl•H2O, and has the following structural formula:

Lidocaine hydrochloride injection, USP in multiple dose vials is a sterile, nonpyrogenic, isotonic, clear, colorless solution containing lidocaine hydrochloride and sodium chloride. Each mL contains 1 mg methylparaben as an antiseptic preservative. The pH of these solutions is adjusted to approximately 6.5 (5.0 to 7.0) with sodium hydroxide and hydrochloric acid.

Ingredients | Strength
Ingredients | 1% | 2%
Ingredients | Amount (Per mL) | Amount (Per mL)
Lidocaine Hydrochloride (Anhydrous) | 10 mg£ | 20 mgµ
Sodium Chloride | 7 mg | 6 mg
Methylparaben | 1 mg | 1 mg
Sodium Hydroxide | Added for pH Adjustment to approximately 6.5 (5.0 to 7.0)
Hydrochloric Acid | Added for pH Adjustment to approximately 6.5 (5.0 to 7.0)

£Quantity is equivalent to 10.7 mg/ mL Lidocaine Hydrochloride, USP (Monohydrate).
μ Quantity is equivalent to 21.4 mg/ mL Lidocaine Hydrochloride, USP (Monohydrate).

Lidocaine hydrochloride injection, USP -MPF is a sterile, nonpyrogenic, isotonic, clear, colorless, and preservative-free solution. The pH of these solutions is adjusted to approximately 6.5 (5.0 to 7.0) with sodium hydroxide and hydrochloric acid.

Ingredients | Strength
Ingredients | 1% | 2%
Ingredients | Amount (Per mL) | Amount (Per mL)
Lidocaine Hydrochloride (Anhydrous) | 10 mg£ | 20 mgµ
Sodium Chloride | 7 mg | 6 mg
Sodium Hydroxide | Added for pH Adjustment to approximately 6.5 (5.0 to 7.0)
Hydrochloric Acid | Added for pH Adjustment to approximately 6.5 (5.0 to 7.0)

£Quantity is equivalent to 10.7 mg/ mL Lidocaine Hydrochloride, USP (Monohydrate).
μ Quantity is equivalent to 21.4 mg/ mL Lidocaine Hydrochloride, USP (Monohydrate).

12 CLINICAL PHARMACOLOGY

12.1 Mechanism of Action

Lidocaine hydrochloride stabilizes the neuronal membrane by inhibiting the ionic fluxes required for the initiation and conduction of impulses thereby effecting local anesthetic action.

12.2 Pharmacodynamics

Excessive blood levels may cause changes in cardiac output, total peripheral resistance, and mean arterial pressure. With central neural blockade these changes may be attributable to block of autonomic fibers, a direct depressant effect of the local anesthetic agent on various components of the cardiovascular system, and/or the beta-adrenergic receptor stimulating action of epinephrine when present. The net effect is normally a modest hypotension when the recommended dosages are not exceeded.

Factors such as acidosis and the use of CNS stimulants and depressants affect the CNS levels of lidocaine hydrochloride required to produce overt systemic effects. Objective adverse manifestations become increasingly apparent with increasing venous plasma levels above 6 mcg free base per mL.

12.3 Pharmacokinetics

Systemic plasma levels of lidocaine following lidocaine hydrochloride injection do not correlate with local efficacy.

Absorption

Information derived from diverse formulations, concentrations and usages reveals that lidocaine hydrochloride is completely absorbed following parenteral administration, its rate of absorption depending, for example, upon various factors such as the site of administration and the presence or absence of a vasoconstrictor agent. Except for intravascular administration, the highest blood levels are obtained following intercostal nerve block and the lowest after subcutaneous administration.

Distribution

The plasma binding of lidocaine hydrochloride is dependent on drug concentration, and the fraction bound decreases with increasing concentration. At concentrations of 1 to 4 mcg of free base per mL 60 to 80 percent of lidocaine hydrochloride is protein bound. Binding is also dependent on the plasma concentration of the alpha-1-acid glycoprotein. Lidocaine hydrochloride crosses the blood-brain and placental barriers, presumably by passive diffusion.

Elimination

The elimination half-life of lidocaine hydrochloride following an intravenous bolus injection is typically 1.5 to 2 hours.

Metabolism

Lidocaine hydrochloride is metabolized rapidly by the liver, and biotransformation includes oxidative N-dealkylation, ring hydroxylation, cleavage of the amide linkage, and conjugation. N-dealkylation, a major pathway of biotransformation, yields the metabolites monoethylglycinexylidide and glycinexylidide. The pharmacological/toxicological actions of these metabolites are similar to, but less potent than, those of lidocaine hydrochloride.

Excretion

Approximately 90% of lidocaine hydrochloride administered is excreted in the form of various metabolites, and less than 10% is excreted unchanged by the kidneys. The primary metabolite in urine is a conjugate of 4-hydroxy-2,6-dimethylaniline.

Specific Populations

Patients with Hepatic Impairment

Because of the rapid rate at which lidocaine hydrochloride is metabolized, any condition that affects liver function may alter lidocaine HCl kinetics. The half-life may be prolonged two-fold or more in patients with liver dysfunction.

Patients with Renal Impairment

Renal dysfunction does not affect lidocaine hydrochloride kinetics but may increase the accumulation of metabolites.

13 NONCLINICAL TOXICOLOGY

13.1 Carcinogenesis, Mutagenesis, Impairment of Fertility

Carcinogenesis

Studies of lidocaine hydrochloride in animals to evaluate the carcinogenic potential have not been conducted.

Mutagenesis

Studies of lidocaine hydrochloride in animals to evaluate the mutagenic potential have not been conducted.

Impairment of Fertility

In a published study, female Sprague-Dawley rats were treated subcutaneously with lidocaine via osmotic pumps starting two weeks prior to mating, and reproductive effects were assessed. Rats dosed up to the high dose of 500 mg/kg/day (approximately 45 times the MRDD on a mg/m2 basis) showed no effects on copulatory rate, pregnancy rate, numbers of corpora lutea, or implantations.

16 HOW SUPPLIED/STORAGE AND HANDLING

Storage: All solutions should be stored at 20°C to 25°C (68°F to 77°F); excursions permitted between 15°C to 30°C (59°F to 86°F) [see USP Controlled Room Temperature]. Protect from light. For single-dose vials and ampules: Discard unused portion. Lidocaine hydrochloride injection, USP. This product is clear and colorless.

Product Code | Unit of Sale | Strength | Each
1% Contains 10 mg lidocaine hydrochloride per mL
0028 | NDC 83854-009-01; Unit of 25 | 500 mg per 50 mL; (10 mg per mL) | NDC 83854-009-25; 50 mL multiple-dose vial
0027 | NDC 83854-009-26; Unit of 25 | 200 mg per 20 mL; (10 mg per mL) | NDC 83854-009-02; 20 mL multiple-dose vial
0187 | NDC 83854-009-27; Unit of 25 | 100 mg per 10 mL; (10 mg per mL) | NDC 83854-009-03; 10 mL multiple-dose vial
2% Contains 20 mg lidocaine hydrochloride per mL
0029 | NDC 83854-010-25; Unit of 25 | 200 mg per 10 mL; (20 mg per mL) | NDC 83854-010-01; 10 mL multiple-dose vial
0030 | NDC 83854-010-26; Unit of 25 | 400 mg per 20 mL; (20 mg per mL) | NDC 83854-010-02; 20 mL multiple-dose vial
0031 | NDC 83854-010-27; Unit of 25 | 1,000 mg per 50 mL; (20 mg per mL) | NDC 83854-010-03; 50 mL multiple-dose vial

Lidocaine hydrochloride injection, USP - MPF. This product is clear and colorless.

Product Code | Unit of Sale | Strength | Each
1% Contains 10 mg lidocaine hydrochloride per mL
0022 | NDC 83854-011-25; Unit of 25 | 20 mg per 2 mL; (10 mg per mL) | NDC 83854-011-01; 2 mL single-dose vial
0023 | NDC 83854-011-26; Unit of 25 | 50 mg per 5 mL; (10 mg per mL) | NDC 83854-011-02; 5 mL single-dose vial
0024 | NDC 83854-011-27; Unit of 25 | 300 mg per 30 mL; (10 mg per mL) | NDC 83854-011-03; 30 mL single-dose vial
2 % Contains 20 mg lidocaine hydrochloride per mL
0025 | NDC 83854-012-25; Unit of 25 | 40 mg per 2 mL; (20 mg per mL) | NDC 83854-012-01; 2 mL single-dose vial
0026 | NDC 83854-012-26; Unit of 25 | 100 mg per 5 mL; (20 mg per mL) | NDC 83854-012-02; 5 mL single-dose vial

17 PATIENT COUNSELING INFORMATION

17.1 Allergic Type Reactions

Assess if the patient has had allergic-type reactions to amide-type local anesthetics or to other formulation ingredients, such as the antimicrobial preservative methylparaben contained in multiple-dose vials [see Contraindications (4), Warnings and Precautions (5.6), Adverse Reactions (6)].

17.3 Methemoglobinemia

Inform patients that use of local anesthetics may cause methemoglobinemia, a serious condition that must be treated promptly. Advise patients or caregivers to stop use and seek immediate medical attention if they or someone in their care experience the following signs or symptoms: pale, gray, or blue colored skin (cyanosis); headache; rapid heart rate; shortness of breath; lightheadedness; or fatigue [see Warnings and Precautions (5.2)].

Manufactured by:
Anthea Pharma Private Limited
Hyderabad, 502307, India

Revised 02/2026

PACKAGE LABEL

PRINCIPAL DISPLAY PANEL - 500 mg/50 mL Vial Label
50 mL Multiple-dose 1%
Lidocaine HCl Injection, USP
500 mg/50 mL (10 mg/mL)

PRINCIPAL DISPLAY PANEL - 500 mg/50 mL Vial Carton
50 mL Multiple-dose Fliptop Vials 1%
Lidocaine HCl Injection, USP
500 mg/50 mL (10 mg/mL)

PACKAGE LABEL – PRINCIPAL DISPLAY – Lidocaine HCl Injection, USP 20 mL Multiple Dose Vial Label
NDC 83854-009-02
Lidocaine HCl Injection, USP
1% 200 mg per 20 mL (10 mg per mL)
For Infiltration and Nerve Block
Not for Caudal or Epidural Use
Rx only
20 mL Multiple Dose Vial

PACKAGE LABEL – PRINCIPAL DISPLAY – Lidocaine HCl Injection, USP 20 mL Multiple Dose Vial Carton Label
NDC 83854-009-26
Lidocaine HCl Injection, USP
1% 200 mg per 20 mL (10 mg per mL)
For Infiltration and Nerve Block
Not for Caudal or Epidural Use
Rx only
25 Multiple Dose Vials, 20 mL

PACKAGE LABEL – PRINCIPAL DISPLAY – Lidocaine HCl Injection, USP 10 mL Multiple Dose Vial Label
NDC 83854-009-03
Lidocaine HCl Injection, USP
1% 100 mg per 10 mL (10 mg per mL)
For Infiltration and Nerve Block
Not for Caudal or Epidural Use
Rx only
10 mL Multiple Dose Vial

PACKAGE LABEL – PRINCIPAL DISPLAY – Lidocaine HCl Injection, USP 10 mL Multiple Dose Vial Carton Label
NDC 83854-009-27
Lidocaine HCl Injection, USP
1% 100 mg per 10 mL (10 mg per mL)
For Infiltration and Nerve Block
Not for Caudal or Epidural Use
Rx only
25 Multiple Dose Vials, 10 mL

PACKAGE LABEL – PRINCIPAL DISPLAY – Lidocaine Hydrochloride Injection, USP 10 mL Multiple Dose Vial Label
NDC 83854-010-01
Lidocaine Hydrochloride Injection, USP
2% 200 mg per 10 mL (20 mg per mL)
For Infiltration and Nerve Block
Not for Caudal or Epidural Use
10 mL Multiple Dose Vial

PACKAGE LABEL – PRINCIPAL DISPLAY – Lidocaine Hydrochloride Injection, USP 10 mL Multiple Dose Vial Carton Label
NDC 83854-010-25
Lidocaine Hydrochloride Injection, USP
2% 200 mg per 10 mL (20 mg per mL)
For Infiltration and Nerve Block
Not for Caudal or Epidural Use
Rx only
25 Multiple Dose Vials, 10 mL

PACKAGE LABEL – PRINCIPAL DISPLAY – Lidocaine Hydrochloride Injection, USP 20 mL Multiple Dose Vial Label
NDC 83854-010-02
Lidocaine Hydrochloride Injection, USP
2% 400 mg per 20 mL (20 mg per mL)
For Infiltration and Nerve Block
Not for Caudal or Epidural Use
20 mL Multiple Dose Vial

PACKAGE LABEL – PRINCIPAL DISPLAY – Lidocaine Hydrochloride Injection, USP 20 mL Multiple Dose Vial Carton Label
NDC 83854-010-26
Lidocaine Hydrochloride Injection, USP
2% 400 mg per 20 mL (20 mg per mL)
For Infiltration and Nerve Block
Not for Caudal or Epidural Use
Rx only
25 Multiple Dose Vials, 20 mL

PACKAGE LABEL – PRINCIPAL DISPLAY – Lidocaine Hydrochloride Injection, USP 50 mL Multiple Dose Vial Label
NDC 83854-010-03
Lidocaine Hydrochloride Injection, USP
2% 1000 mg per 50 mL (20 mg per mL)
For Infiltration and Nerve Block
Not for Caudal or Epidural Use
50 mL Multiple Dose Vial

PACKAGE LABEL – PRINCIPAL DISPLAY – Lidocaine Hydrochloride Injection, USP 50 mL Multiple Dose Vial Carton Label
NDC 83854-010-27
Lidocaine Hydrochloride Injection, USP
2% 1000 mg per 50 mL (20 mg per mL)
For Infiltration and Nerve Block
Not for Caudal or Epidural Use
Rx only
25 Multiple Dose Vials, 50 mL

PACKAGE LABEL – PRINCIPAL DISPLAY – Lidocaine Hydrochloride Injection – MPF 2 mL Single Dose Vial Label
NDC 83854-011-01
Lidocaine Hydrochloride Injection, USP - MPF
1% 20 mg per 2 mL (10 mg per mL)
For Infiltration and Nerve Block Including Caudal and Epidural Use.
2 mL Single Dose Vial

PACKAGE LABEL – PRINCIPAL DISPLAY – Lidocaine Hydrochloride Injection – MPF 2 mL Single Dose Vial Carton Panel
NDC 83854-011-25
Lidocaine Hydrochloride Injection, USP - MPF
1% 20 mg per 2 mL (10 mg per mL)
For Infiltration and Nerve Block Including Caudal and Epidural Use.
Methylparaben Free
25 Single Dose Vials, 2 mL
Rx only

PACKAGE LABEL – PRINCIPAL DISPLAY – Lidocaine HCl Injection, USP – MPF 5 mL Single Dose Vial Label
NDC 83854-011-02
Lidocaine HCl Injection, USP- MPF
1% 50 mg per 5 mL (10 mg per mL)
For Infiltration and Nerve Block Including Caudal and Epidural Use.
Methylparaben Free
5 mL Single Dose Vial
Rx only

PACKAGE LABEL – PRINCIPAL DISPLAY – Lidocaine HCl Injection, USP – MPF 5 mL Single Dose Vial Carton Label
NDC 83854-011-26
Lidocaine HCl Injection, USP- MPF (lidocaine HCl Injection, USP)
1% 50 mg per 5 mL (10 mg per mL)
For Infiltration and Nerve Block Including Caudal and Epidural Use.
Methylparaben Free
Rx only
25 Single Dose Vials, 5 mL

PACKAGE LABEL – PRINCIPAL DISPLAY – Lidocaine HCl Injection, USP – MPF 30 mL Single Dose Vial Label
NDC 83854-011-03
Lidocaine HCl Injection, USP- MPF
1% 300 mg per 30 mL (10 mg per mL)
For Infiltration and Nerve Block Including Caudal and Epidural Use.
Methylparaben Free
30 mL Single Dose Vial
Rx only

PACKAGE LABEL – PRINCIPAL DISPLAY – Lidocaine HCl Injection, USP – MPF 30 mL Single Dose Vial Carton Label
NDC 83854-011-27
Lidocaine HCl Injection, USP- MPF
1% 300 mg per 30 mL (10 mg per mL)
For Infiltration and Nerve Block Including Caudal and Epidural Use.
Methylparaben Free
Rx only
25 Single Dose Vials, 30 mL

PACKAGE LABEL – PRINCIPAL DISPLAY – Lidocaine Hydrochloride Injection, USP - MPF 2 mL Single Dose Vial Label
NDC 83854-012-01
Lidocaine Hydrochloride Injection, USP
2% 40 mg per 2 mL (20 mg per mL)
For Infiltration and Nerve Block Including Caudal and Epidural Use.
2 mL Single Dose Vial

PACKAGE LABEL – PRINCIPAL DISPLAY – Lidocaine Hydrochloride Injection, USP – MPF 2 mL Single Dose Vial Carton Panel
NDC 83854-012-25
Lidocaine Hydrochloride Injection, USP
2% 40 mg per 2 mL (20 mg per mL)
For Infiltration and Nerve Block Including Caudal and Epidural Use.
Methylparaben Free
25 Single Dose Vials, 2 mL
Rx only

PACKAGE LABEL – PRINCIPAL DISPLAY – Lidocaine Hydrochloride Injection, USP – MPF 5 mL Single Dose Vial Label
NDC 83854-012-02
Lidocaine Hydrochloride Injection, USP
2% 100 mg per 5 mL (20 mg per mL)
For Infiltration and Nerve Block Including Caudal and Epidural Use.
Methylparaben Free
5 mL Single Dose Vial
Rx only

PACKAGE LABEL – PRINCIPAL DISPLAY – Lidocaine Hydrochloride Injection, USP – MPF 5 mL Single Dose Vial Carton Label
NDC 83854-012-26
Lidocaine Hydrochloride Injection, USP
2% 100 mg per 5 mL (20 mg per mL)
For Infiltration and Nerve Block Including Caudal and Epidural Use.
Methylparaben Free
Rx only
25 Single Dose Vials, 5 mL